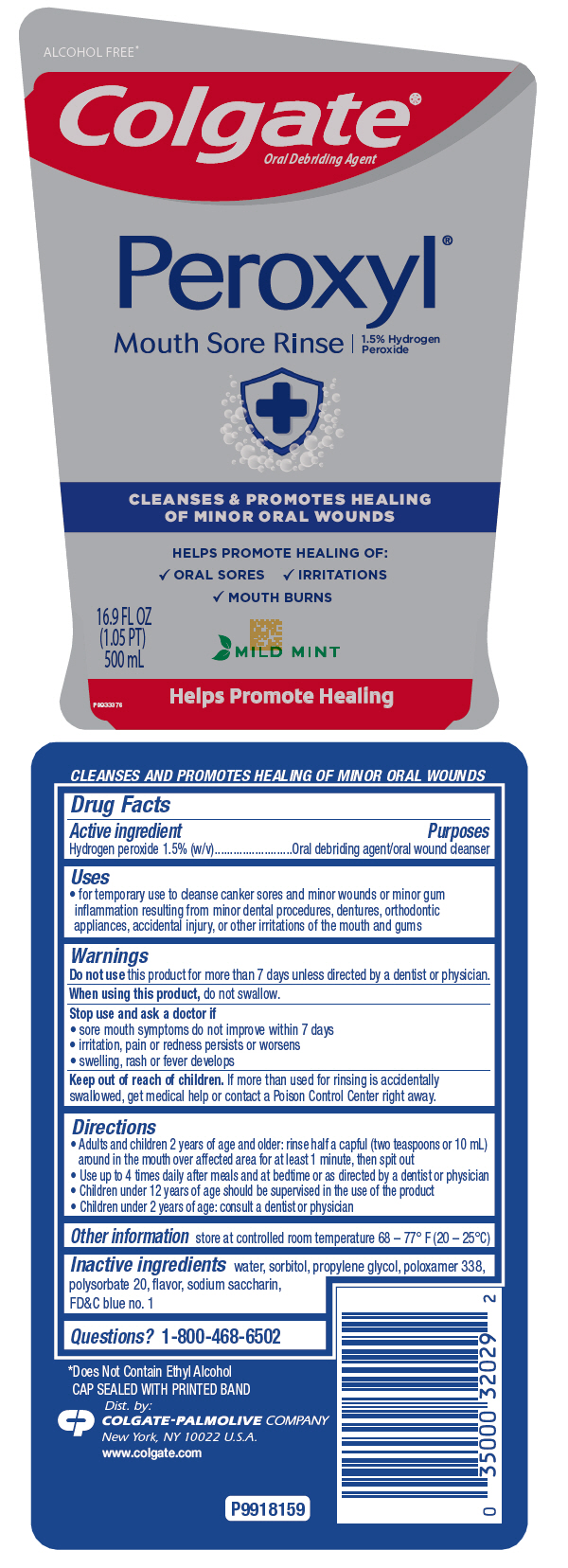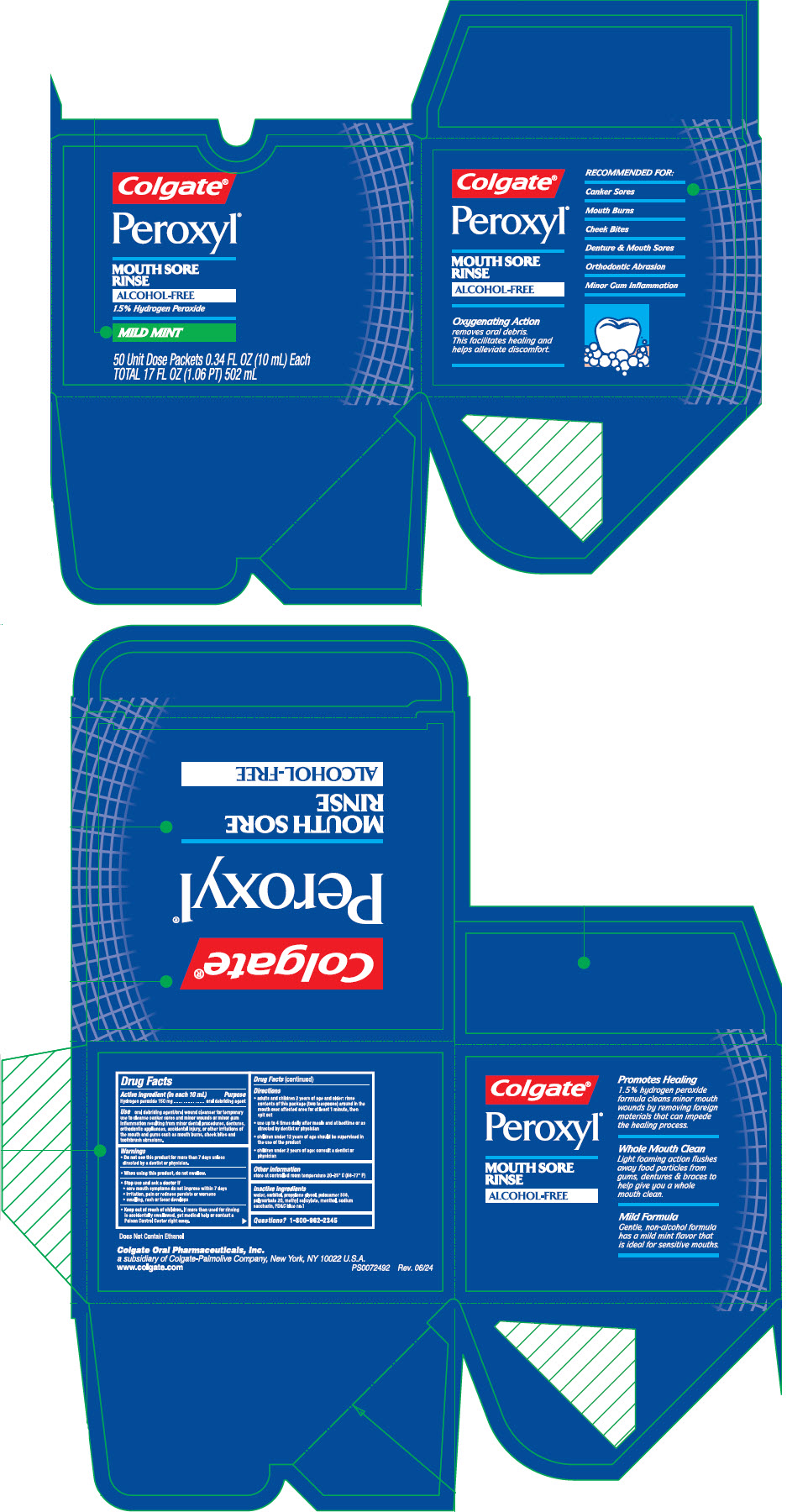 DRUG LABEL: Peroxyl Mouth Sore  Mild Mint
NDC: 0126-0083 | Form: RINSE
Manufacturer: Colgate Oral Pharmaceuticals Inc.
Category: otc | Type: HUMAN OTC DRUG LABEL
Date: 20241125

ACTIVE INGREDIENTS: HYDROGEN PEROXIDE 15 mg/1 mL
INACTIVE INGREDIENTS: WATER; SORBITOL; PROPYLENE GLYCOL; POLOXAMER 338; POLYSORBATE 20; SACCHARIN SODIUM; FD&C BLUE NO. 1

Peroxyl® Mouth Sore Mild Mint

Drug Facts

Active ingredient

Hydrogen peroxide 1.5% (w/v)

Purposes

Oral debriding agent/oral wound cleanser

Uses

- for temporary use to cleanse canker sores and minor wounds or minor gum inflammation resulting from minor dental procedures, dentures, orthodontic appliances, accidental injury, or other irritations of the mouth and gums

Warnings

Do not use this product for more than 7 days unless directed by a dentist or physician.

When using this product, do not swallow.

Stop use and ask a doctor if

- sore mouth symptoms do not improve within 7 days
- irritation, pain or redness persists or worsens
- swelling, rash or fever develops

Keep out of reach of children. If more than used for rinsing is accidentally swallowed, get medical help or contact a Poison Control Center right away.

Directions

- Adults and children 2 years of age and older: rinse half a capful (two teaspoons or 10 mL) around in the mouth over affected area for at least 1 minute, then spit out
- Use up to 4 times daily after meals and at bedtime or as directed by a dentist or physician
- Children under 12 years of age should be supervised in the use of the product
- Children under 2 years of age: consult a dentist or physician

Inactive ingredients

water, sorbitol, propylene glycol, poloxamer 338, polysorbate 20, flavor, sodium saccharin, FD&C blue no. 1

Other Information

store at controlled room temperature 68 – 77° F (20 – 25°C)

Questions?

1-800-468-6502

Dist. by:
COLGATE-PALMOLIVE COMPANY
New York, NY 10022

PRINCIPAL DISPLAY PANEL - 500 mL Bottle Label

ALCOHOL FREE*

Colgate®
Oral Debriding Agent

Peroxyl®

Mouth Sore Rinse |
1.5% Hydrogen
Peroxide

CLEANSES & PROMOTES HEALING
OF MINOR ORAL WOUNDS

HELPS PROMOTE HEALING OF:

✓ ORAL SORES
✓ IRRITATIONS
✓ MOUTH BURNS

MILD MINT

16.9 FL OZ
(1.05 PT)
500 mL

Helps Promote Healing

P9933376

PRINCIPAL DISPLAY PANEL - 50 Dose Packet Carton

Colgate®

Peroxyl®

MOUTH SORE
RINSE
ALCOHOL-FREE
1.5% Hydrogen Peroxide

MILD MINT

50 Unit Dose Packets 0.34 FL OZ (10 mL) Each
TOTAL 17 FL OZ (1.06 PT) 502 mL